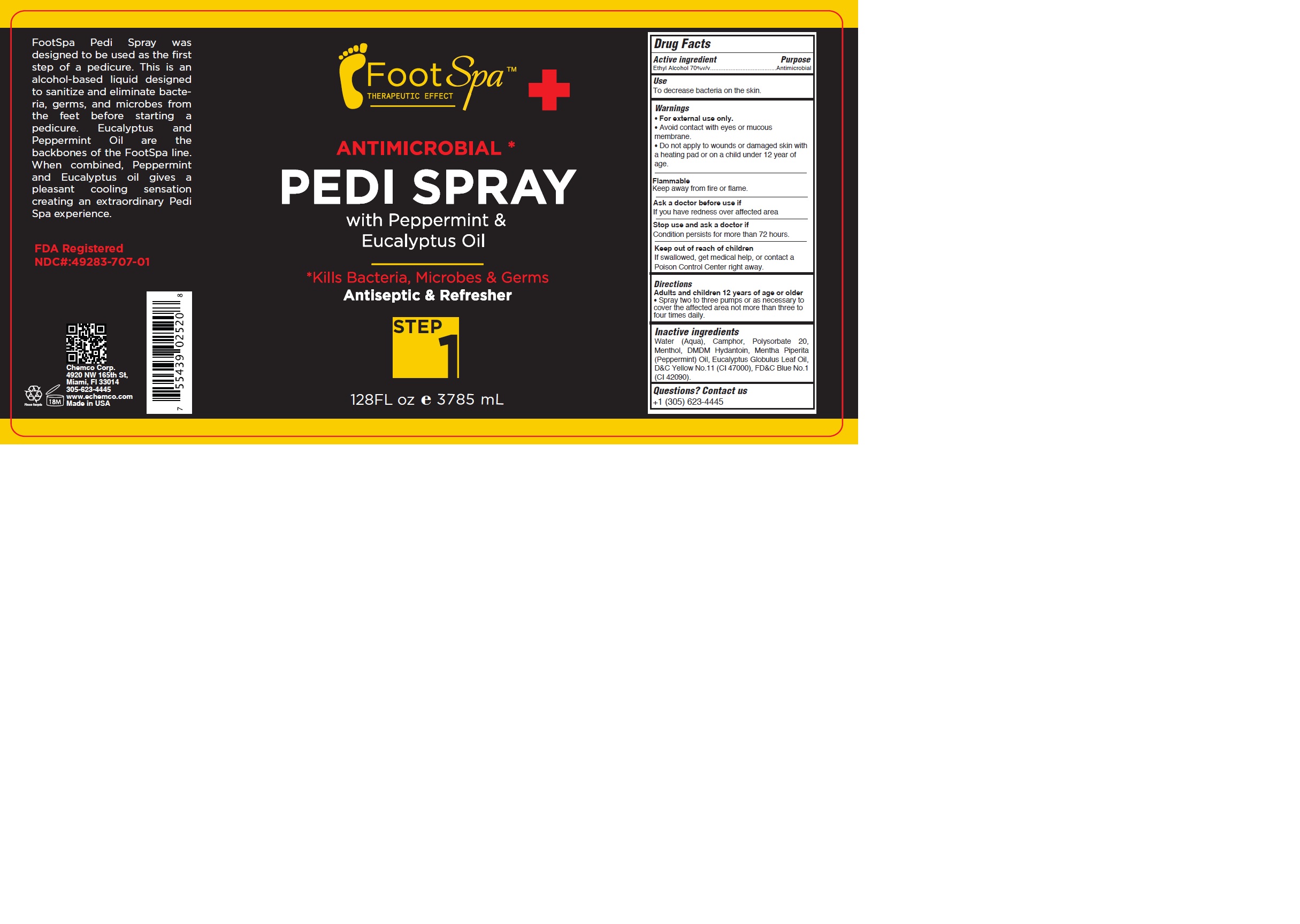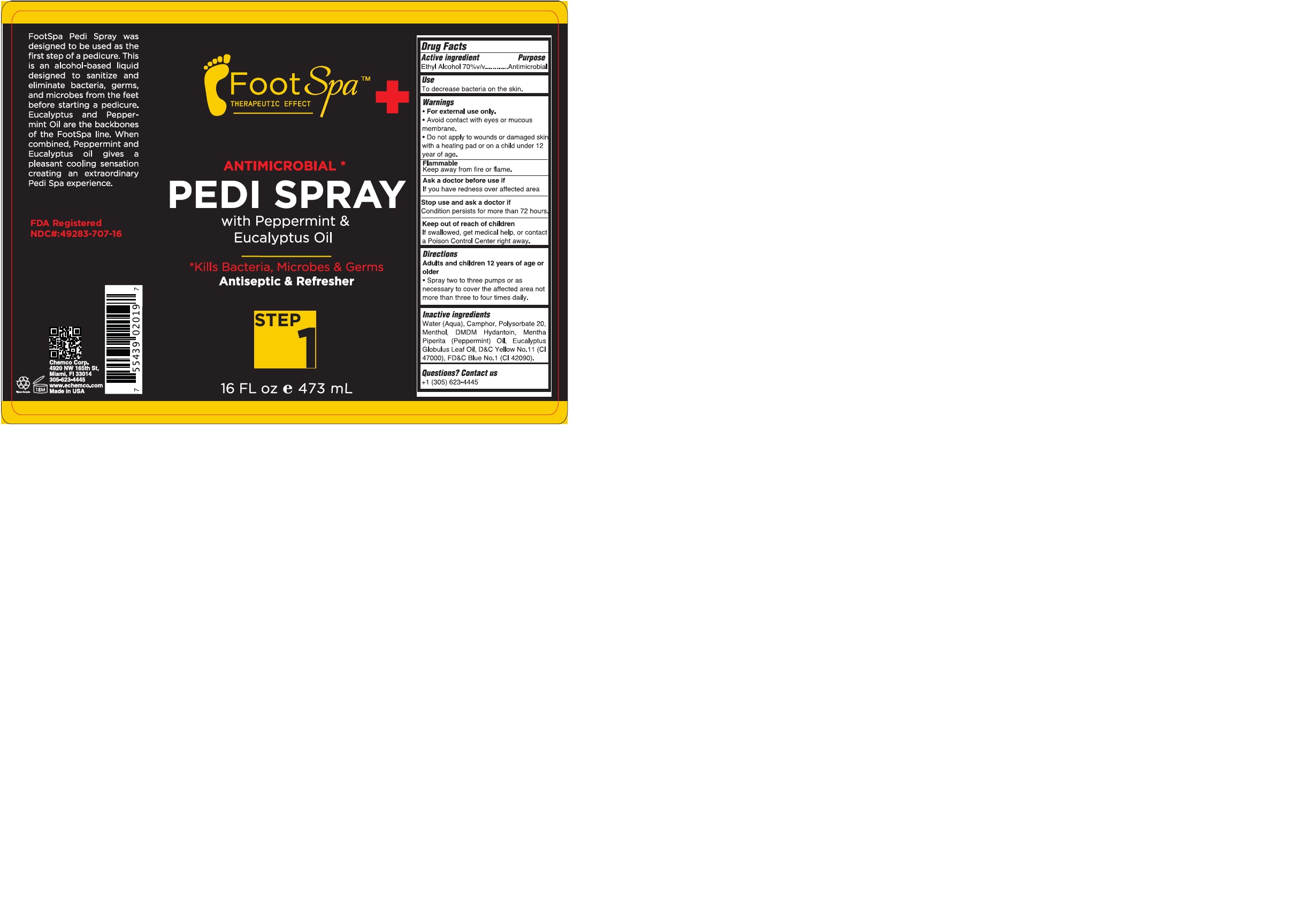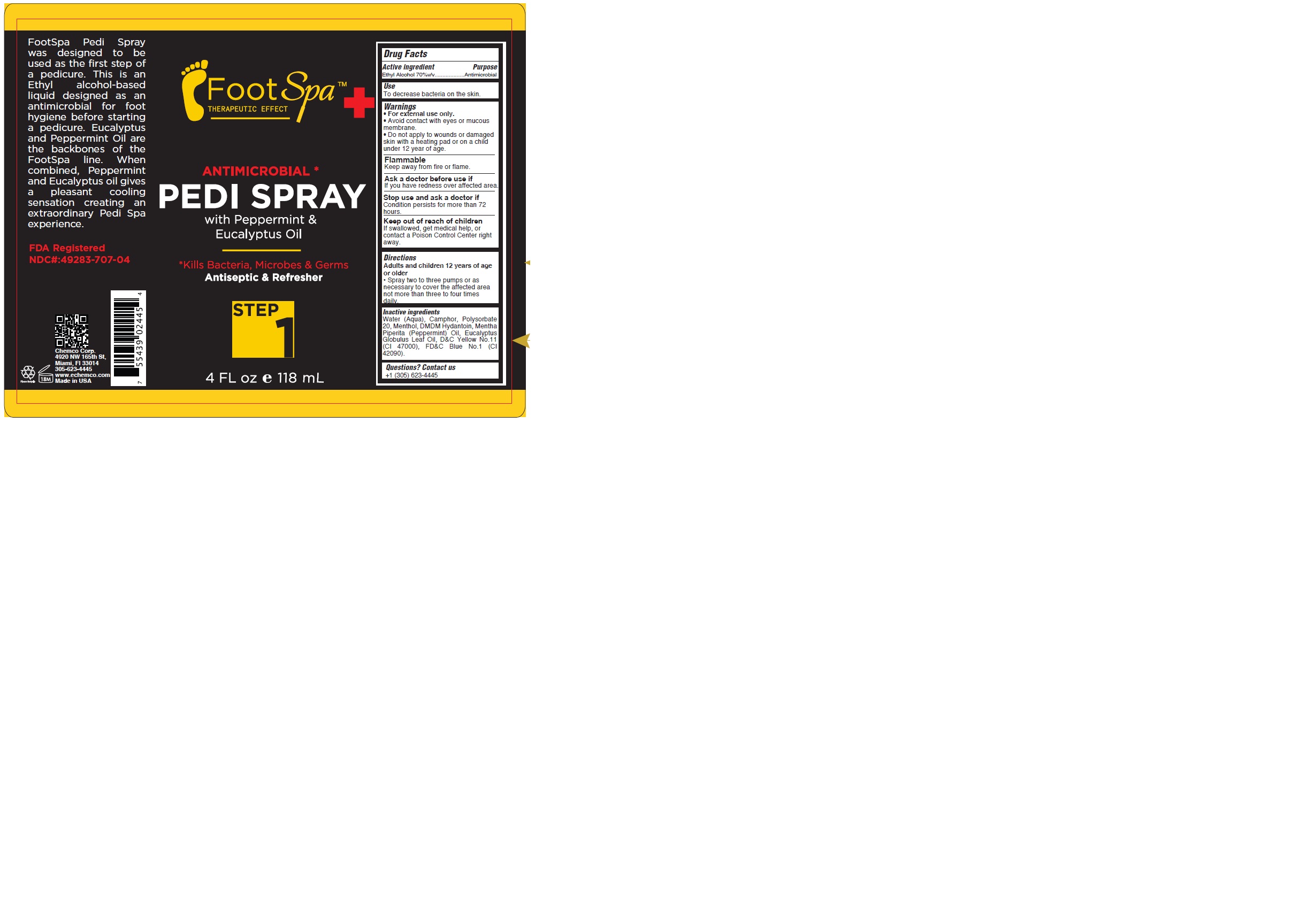 DRUG LABEL: FOOTSPA PEDI
NDC: 49283-707 | Form: SPRAY
Manufacturer: CHEMCO CORPORATION
Category: otc | Type: HUMAN OTC DRUG LABEL
Date: 20251108

ACTIVE INGREDIENTS: ALCOHOL 70 mL/100 mL
INACTIVE INGREDIENTS: WATER; POLYSORBATE 20; MENTHOL; FD&C BLUE NO. 1; CAMPHOR (SYNTHETIC); PEPPERMINT OIL; EUCALYPTUS OIL; D&C YELLOW NO. 11; DMDM HYDANTOIN

49283-707-16
49283-707-04
49283-707-01

ACTIVE INGREDIENT

Ethyl Alcohol 70%v/v

PURPOSE

Antimicrobial

USES:

To decrease bacteria on the skin.

WARNINGS

• For external use only.

• Avoid contact with eyes or mucous membrane.

• Do not apply to wounds or damaged
skin with a heating pad or on a child
under 12 year of age.

FLAMMABLE:

Keep away from fire or flame.

ASK A DOCTOR BEFORE USE IF

If you have redness over affected area.

STOP USE

Condition persists for more than 72 hours.

KEEP OUT OF REACH OF CHILDREN

If swallowed, get medical help, or contact a Poison Control Center right away.

DIRECTIONS:

Adults and children 12 years of age or older
• Spray two to three pumps or as
necessary to cover the affected area
not more than three to four times
daily.

INACTIVE INGREDIENT

Water (Aqua), Camphor, Polysorbate 20, Menthol, DMDM Hydantoin, Mentha Piperita (Peppermint) Oil, Eucalyptus Globulus Leaf Oil, D&C Yellow No.11(CI 47000), FD&C Blue No.1 (CI 42090).

QUESTIONS

Contact us
+1 (305) 623-4445